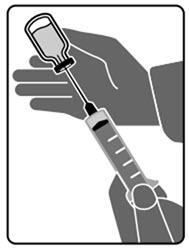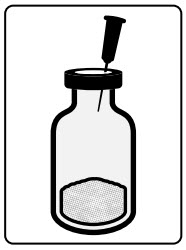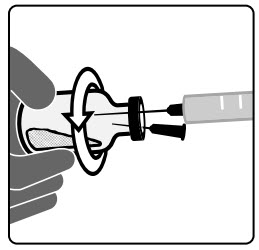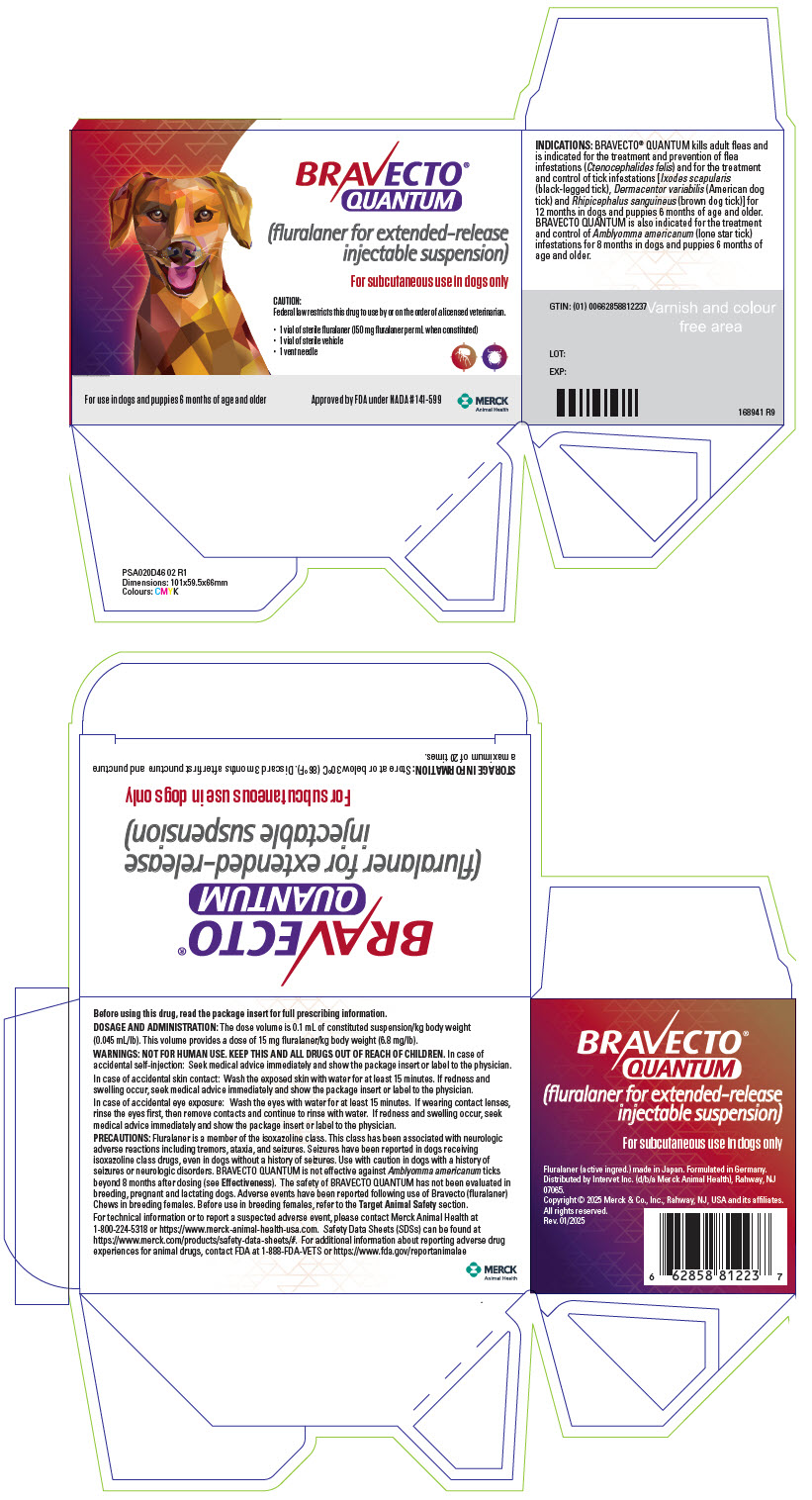 DRUG LABEL: Bravecto Quantum
NDC: 0061-1438 | Form: KIT | Route: SUBCUTANEOUS
Manufacturer: Merck Sharp & Dohme Corp.
Category: animal | Type: PRESCRIPTION ANIMAL DRUG LABEL
Date: 20250715

ACTIVE INGREDIENTS: FLURALANER 150 mg/1 1

BRAVECTO®
QUANTUM
(fluralaner for extended-release injectable suspension)

150 mg fluralaner per mL when constituted

For subcutaneous use in dogs only

CAUTION:

Federal law restricts this drug to use by or on the order of a licensed veterinarian.

DESCRIPTION:

BRAVECTO® QUANTUM (fluralaner for extended-release injectable suspension) is an aqueous suspension consisting of two individual vials that require mixing prior to administration. One vial contains fluralaner powder and the second vial contains sterile vehicle for constitution with the powder.

Each mL of constituted drug product contains 150 mg fluralaner, 20 mg carboxymethylcellulose sodium, 20 mg benzyl alcohol, 7 mg dibasic sodium phosphate dihydrate, 1 mg poloxamer 124, and water for injection. Hydrochloric acid and sodium hydroxide are used to adjust pH.

The chemical name of fluralaner is (±)-4-[5-(3,5-dichlorophenyl)-5-(trifluoromethyl)-4,5-dihydroisoxazol-3-yl]-2-methyl-N-[2-oxo-2-(2,2,2-trifluoroethylamino)ethyl]benzamide.

INDICATIONS:

BRAVECTO QUANTUM kills adult fleas and is indicated for the treatment and prevention of flea infestations (Ctenocephalides felis) and for the treatment and control of tick infestations [Ixodes scapularis (black-legged tick), Dermacentor variabilis (American dog tick) and Rhipicephalus sanguineus (brown dog tick)] for 12 months in dogs and puppies 6 months of age and older.

BRAVECTO QUANTUM is also indicated for the treatment and control of Amblyomma americanum (lone star tick) infestations for 8 months in dogs and puppies 6 months of age and older.

DOSAGE AND ADMINISTRATION:

Frequency of Treatment:

BRAVECTO QUANTUM should be administered as a single subcutaneous dose every 12 months.

BRAVECTO QUANTUM should be administered every 8 months in the case of potential exposure to Amblyomma americanum ticks (see Effectiveness).

Dose:

The subcutaneous dose volume is 0.1 mL of the constituted suspension/kg body weight (0.045 mL/lb). This volume provides a dose of 15 mg fluralaner/kg body weight (6.8 mg/lb). The dog should be weighed at the time of dosing to calculate an accurate dose. The following table provides a guide to weight specific dose volumes.

Guide to Body Weight Specific Dose Volumes [All dogs should be dosed at 0.1 mL suspension/kg body weight (0.045 mL/lb).]
Body Weight (lb) | Body Weight (kg) | Dose Volume (mL)
2.2 lb | 1 kg | 0.1 mL
11 lb | 5 kg | 0.5 mL
22 lb | 10 kg | 1.0 mL
33 lb | 15 kg | 1.5 mL
44 lb | 20 kg | 2.0 mL
55 lb | 25 kg | 2.5 mL
66 lb | 30 kg | 3.0 mL
77 lb | 35 kg | 3.5 mL
88 lb | 40 kg | 4.0 mL
99 lb | 45 kg | 4.5 mL
110 lb | 50 kg | 5.0 mL
121 lb | 55 kg | 5.5 mL
132 lb | 60 kg | 6.0 mL

Treatment with BRAVECTO QUANTUM may begin at any time of the year and can continue year-round without interruption.

Constitution Procedures:

BRAVECTO QUANTUM must be prepared prior to the first use by adding the sterile vehicle to the fluralaner powder (see Constitution Procedures).

Administration Instructions:

For subcutaneous injection only. Do not administer by any other route.

1. The fluralaner powder will separate out of suspension upon standing. Before every use, shake the constituted vial vigorously for 30 seconds prior to drawing up a dose to achieve a uniform suspension.
2. Withdraw 0.1 mL of constituted suspension/kg of body weight (0.045 mL/lb) into an appropriately sized sterile syringe fitted with an 18 G needle.
3. Use another 18 G needle for dosing. Administer the dose within 2 minutes after drawing it into the dosing syringe to maintain a uniform suspension and accurate dosing. Discard if syringe sits more than 2 minutes. The dose sitting in the syringe beyond 2 minutes may decrease effectiveness.
4. Inject the product subcutaneously in the dorsoscapular region.

CONTRAINDICATIONS:

There are no known contraindications for the use of the product.

WARNINGS:

User Safety Warnings:

Not for use in humans. Keep this and all drugs out of reach of children.

In case of accidental self-injection:

- Seek medical advice immediately and show the package insert or label to the physician.

In case of accidental skin contact:

- Wash the exposed skin with water for at least 15 minutes.
- If redness and swelling occur, seek medical advice immediately and show the package insert or label to the physician.

In case of accidental eye exposure:

- Wash the eyes with water for at least 15 minutes.
- If wearing contact lenses, rinse the eyes first, then remove contacts and continue to rinse with water.
- If redness and swelling occur, seek medical advice immediately and show the package insert or label to the physician.

PRECAUTIONS:

Fluralaner is a member of the isoxazoline class. This class has been associated with neurologic adverse reactions including tremors, ataxia, and seizures. Seizures have been reported in dogs receiving isoxazoline class drugs, even in dogs without a history of seizures. Use with caution in dogs with a history of seizures or neurologic disorders.

BRAVECTO QUANTUM is not effective against Amblyomma americanum ticks beyond 8 months after dosing (see Effectiveness).

Prior to administration of BRAVECTO QUANTUM, owners should be informed that this product may take 3-5 days to see a notable reduction in ticks (see Effectiveness).

Hypersensitivity reactions, including anaphylaxis, have been reported with the use of this product and should be treated immediately with the same measures used to treat hypersensitivity reactions to vaccines and other injectable products (see Adverse Reactions).

The safety and effectiveness of BRAVECTO QUANTUM has not been evaluated in dogs less than 6 months of age.

The safety of BRAVECTO QUANTUM has not been evaluated in breeding, pregnant and lactating dogs. Reproductive adverse events have been reported following use of Bravecto (fluralaner) Chews in breeding females including birth defects (including limb deformities and cleft palate), stillbirth, and abortion.

Before use in breeding female dogs, refer to the Target Animal Safety section.

ADVERSE REACTIONS:

In a well-controlled U.S. field study, 225 dogs were administered two doses of BRAVECTO QUANTUM at a 1-year interval and 96 dogs were administered an oral active control every 12 weeks for a total of 6 doses. Over the 455-day study period, all observations of potential adverse reactions were recorded.

Percentage of Dogs with Adverse Reactions in the Field Study
Adverse Reaction (AR) | BRAVECTO QUANTUM (n = 225 dogs) | Active Control (n = 96 dogs)
Lethargy | 4.9% | 3.1%
Decreased appetite | 4.4% | 4.2%
Vomiting | 4.0% | 0%
Diarrhea | 2.7% | 3.1%
Liver enzymes (serum ALT or ALP) greater than twice the upper reference range [Alanine aminotransferase (ALT); Alkaline phosphatase (ALP)] | 2.7% | 2.1%
Pruritus | 1.8% | 2.1%
Injection site lumps or swelling [Mild injection site reactions, described as a lump, bump or knot, occurred in three BRAVECTO QUANTUM treated dogs and were all observed within 3 days of the injection. All injection site reactions were self-limiting and resolved following 1, 4, and 27 days after the initial observation.] | 1.3% | 0%
Seizures [Two dogs treated with BRAVECTO QUANTUM experienced seizures during the study. One dog with a history of at least one seizure within three months prior to the start of the study, reported 6 seizures in 9 months starting 23 days after the initial dose. Although anticonvulsant medications were not started, no additional seizures were observed during the study following the second dose administered 12 months after the initial dose. A second dog reported 8 seizures starting 57 days after the initial dose. The dog was removed from the study on Day 84 and managed with anticonvulsant medications.] | 0.9% | 0%

One dog treated in the BRAVECTO QUANTUM group had a hypersensitivity reaction which included hives, facial edema, vomiting, and heavy breathing within the first 12 hours following the initial treatment. The dog was treated with oral antihistamines and recovered within 24 hours of treatment. No additional hypersensitivity reactions were observed in subsequent dosing 12 months later when premedicated with diphenhydramine.

In well-controlled foreign laboratory effectiveness studies, after administration of BRAVECTO QUANTUM, two dogs exhibited slight mucosal hyperemia the day following administration that resolved the following day, one dog exhibited transient erythema 10 minutes post-injection that resolved within 1 hour, and one dog had a nonpainful swollen upper eyelid observed 24 hours post treatment. In a large European field study, pain on injection of BRAVECTO QUANTUM was reported in 5 dogs.

Foreign Market Experience:

The following adverse events were reported voluntarily during post-approval use of BRAVECTO QUANTUM in foreign markets: gastrointestinal reactions (including vomiting, diarrhea, decreased appetite, and acute hemorrhagic diarrhea syndrome), lethargy, injection site reactions (including swelling, lump, pain, bleeding, and abscess), immune-mediated disorders (including hypersensitivity reactions, anaphylaxis, and immune-mediated hemolytic anemia), pruritus, dermatitis, and neurologic reactions (including seizures, ataxia, and tremors).

CONTACT INFORMATION:

For technical information or to report a suspected adverse event, please contact Merck Animal Health at 1-800-224-5318 or https://www.merck-animal-health-usa.com. Safety Data Sheets (SDSs) can be found at https://www.merck.com/products/safety-data-sheets/#. For additional information about reporting adverse drug experiences for animal drugs, contact FDA at 1-888-FDA-VETS or https://www.fda.gov/reportanimalae

CLINICAL PHARMACOLOGY:

Mechanism of Action:

Fluralaner is for systemic use and belongs to the class of isoxazoline-substituted benzamide derivatives. Fluralaner is an inhibitor of the arthropod nervous system. The mode of action of fluralaner is the antagonism of the ligand-gated chloride channels (gamma-aminobutyric acid (GABA)-receptor and glutamate-receptor).

Pharmacokinetics:

The pharmacokinetics of fluralaner were evaluated in 4 male and 4 female Beagle dogs receiving a single dose of 15 mg/kg BRAVECTO QUANTUM subcutaneously. Blood samples were collected predose and 32 times post-dose for 450 days. Systemic concentrations were measurable until study termination on Day 450.

Mean (± standard deviation) Plasma Pharmacokinetic Parameters of Fluralaner
Parameter | Estimate
Cmax (ng/mL) | 775 ± 179
Clast (ng/mL) | 79.5 ± 47.4
Tmax [Median and Range] (day) | 36 (29 - 71)
AUClast (day*ng/mL) | 139000 ± 28600
AUCinf (day*ng/mL) | 158000 ± 31400
t1/2 (day) | 130 ± 27.1
Cmax = maximum plasma concentration
Clast = plasma concentration on Day 450
Tmax = time to maximum plasma concentration
AUClast = area under the curve from the time of dosing to the last quantifiable plasma concentration
AUCinf = area under the curve from the time of dosing extrapolated to infinity
t½ = half-life

Following 6 doses of BRAVECTO QUANTUM administered subcutaneously every 4 months to 24 Beagle dogs at doses of 15 (1X), 45 (3X), and 75 (5X) mg/kg, AUC and Cmax were proportional over the dose range. Significant accumulation occurred with ratios of 3.9, 4.6, and 3.5 for the 1X, 3X, and 5X groups, respectively. Steady state was reached by the fourth dose (357 days) in the 1X and 3X groups and by the third dose (238 days) in the 5X group.

EFFECTIVENESS:

Treatment and Prevention of Flea Infestations:

In well-controlled laboratory studies, BRAVECTO QUANTUM was 100% effective against adult fleas by 48 hours after treatment and ≥ 99.7% effective against adult fleas 24 hours post-infestation from one week through 12 months after treatment.

In a well-controlled 455-day U.S. field study conducted in households with existing flea infestations, the effectiveness of BRAVECTO QUANTUM against fleas when administered at 12-month intervals was ≥ 99.2% for 12 months. Dogs with signs of flea allergy dermatitis showed improvement in erythema, alopecia, papules, scales, crusts, and excoriation as a direct result of eliminating flea infestations.

Treatment and Control of Tick Infestations:

In a well-controlled laboratory study, the onset of effectiveness (≥ 90.0%) against preexisting infestations occurred within 3 days following post-treatment for Dermacentor variabilis and Ixodes scapularis, and within 4 days post-treatment for Rhipicephalus sanguineus. In well-controlled laboratory studies, BRAVECTO QUANTUM demonstrated ≥ 94.0% effectiveness against Rhipicephalus sanguineus ticks 48-hours post-infestation starting one week through 12 months after treatment.

In well-controlled laboratory studies, fluralaner, the active ingredient in BRAVECTO QUANTUM, demonstrated effectiveness against Ixodes scapularis and Dermacentor variabilis.

In a well-controlled laboratory study, the onset of effectiveness (≥ 90.0%) against preexisting Amblyomma americanum infestations occurred 5 days post-treatment. In well-controlled laboratory studies, BRAVECTO QUANTUM demonstrated > 93.5% effectiveness against Amblyomma americanum at 72-hours post-infestation starting approximately one week through 8 months after treatment but failed to demonstrate effectiveness beyond 8 months.

TARGET ANIMAL SAFETY:

Margin of Safety Study:

In a margin of safety study, 32 healthy intact Beagle dogs (4 dogs/sex/group) aged 6 months were administered BRAVECTO QUANTUM by subcutaneous injection at doses of 0 (0X), 15 (1X), 45 (3X), or 75 (5X) mg/kg every 4 months for a total of 6 doses (Days 1, 120, 239, 358, 477 and 596). Dogs in the control group (0X) were injected with sterile saline. Two dogs died during the study. One male in the 3X group was euthanized due to a prolapsed rectum and replaced on Day 15. One male in the 3X group was euthanized on Day 475 due to seizures. Necropsy determined this dog died of polyarteritis. The administration of BRAVECTO QUANTUM resulted in dose-volume dependent injection site swellings that resolved over time. Injection site swellings in the 1X group lasted up to 32 days after the first injection, up to 62 days after the second injection, and persisted in some dogs throughout the dosing interval after the third through sixth injections. Injection site swellings in the 3X and 5X groups occurred after each injection and persisted in some dogs throughout the dosing interval. No pain was observed during any injection site assessment. Occasional erythema occurred in all treatment groups, including dogs in the control group. Abnormal macroscopic changes at the injection sites included accumulation of tan material only in the dogs administered BRAVECTO QUANTUM. On histopathology, abnormal microscopic observation of the injection sites in dogs administered BRAVECTO QUANTUM included fibrosis (minimal to moderate), granulomatous inflammation (minimal to moderate), and/or histiocytic infiltration (minimal).

Reproductive Safety Study:

Reproductive safety was evaluated for Bravecto Chews, NADA 141-426. Bravecto Chews contains fluralaner, the same active ingredient as in BRAVECTO QUANTUM. Bravecto Chews was administered orally to intact, reproductively-sound male and female Beagle dogs at a dose of up to 168 mg/kg on three to four occasions at 8-week intervals. The dogs in the control group were untreated. There were no clinically-relevant, treatment-related effects on the body weights, food consumption, reproductive performance, semen analysis, litter data, gross necropsy (adult dogs) or histopathology findings (adult dogs and puppies).

One adult dog in the treated group suffered a seizure during the course of the study (46 days after the third treatment). Abnormal salivation was observed on 17 occasions: in six treated dogs (11 occasions) after dosing and four control dogs (6 occasions).

The following abnormalities were noted in 7 pups from 2 of the 10 dams in only the treated group during gross necropsy examination: limb deformity (4 pups), enlarged heart (2 pups), enlarged spleen (3 pups), and cleft palate (2 pups). During veterinary examination at Week 7, two pups from the control group had inguinal testicles, and two and four pups from the treated group had inguinal and cryptorchid testicles, respectively. No undescended testicles were observed at the time of necropsy (Days 50 to 71).

In a well-controlled field study BRAVECTO QUANTUM was used concurrently with other medications, such as vaccines, anthelmintics, antibiotics (including topicals), steroids, analgesics, and anesthetics. No adverse reactions were observed from the concurrent use of BRAVECTO QUANTUM with other medications.

CONSTITUTION PROCEDURES:

Items needed to constitute BRAVECTO QUANTUM

- Fluralaner powder vial – included
- Sterile vehicle vial – included
- Vent needle (25 G) – included
- Sterile transfer needle (18 G) – not included
- Sterile 20 mL syringe for transfer – not included

Step 1

Step 2

Step 3

Constitution of the Product Vial:

BRAVECTO QUANTUM is supplied in 2 vials that must be combined prior to administration.

1. Shake the fluralaner powder vial to break up any aggregates prior to constitution.
2. Prior to use, invert the vehicle vial at least 3 times until visibly uniform. The vehicle solution may be clear to cloudy in appearance.
3. Using an 18 G needle and syringe, first inject up to 14 mL of air into the vehicle vial, then withdraw 15 mL of the vehicle from the vial (Step 1). There is more vehicle supplied in the vial than required for constitution.
4. Insert the 25 G vent needle into the top of the fluralaner powder vial (Step 2).
5. While rotating the vial horizontally in hand, slowly transfer the vehicle into the fluralaner powder vial to ensure complete wetting of the powder (Step 3).
6. Once the vehicle has been added, remove the vent and transfer needles from the fluralaner powder vial. Discard needles.
7. Shake the vial vigorously for at least 30 seconds until a thoroughly mixed suspension of the fluralaner powder and vehicle is produced.
8. The fluralaner powder will separate out of suspension upon standing. Before every use, shake the constituted vial vigorously for 30 seconds prior to drawing up a dose to achieve a uniform suspension.
9. Withdraw 0.1 mL of constituted suspension/kg of body weight (0.045 mL/lb) into an appropriately sized sterile syringe fitted with an 18 G needle (see Dosage and Administration).
10. Use another 18 G needle for dosing. Administer the dose within 2 minutes after drawing it into the dosing syringe to maintain a uniform suspension and accurate dosing. Discard if syringe sits more than 2 minutes. The dose sitting in the syringe beyond 2 minutes may decrease effectiveness.
11. Inject the product subcutaneously in the dorsoscapular region.
12. Discard 3 months after first puncture. Puncture a maximum of 20 times.

STORAGE CONDITIONS:

Store at or below 30°C (86°F). Discard 3 months after first puncture and puncture a maximum of 20 times.

HOW SUPPLIED:

BRAVECTO QUANTUM (fluralaner for extended-release injectable suspension) 20 mL vial product is available in a 1-pack presentation that includes one vial containing 2.51 grams of sterile fluralaner and one vial containing the required 15 mL of sterile vehicle for constitution.

Approved by FDA under NADA # 141-599

Formulated in Germany.
Distributed by Intervet Inc. (d/b/a Merck Animal Health), Rahway, NJ 07065.
Copyright © 2025 Merck & Co., Inc., Rahway, NJ, USA and its affiliates. All rights reserved.

Rev. 01/2025

168621 R10

PRINCIPAL DISPLAY PANEL - Kit Carton

BRAVECTO®
QUANTUM
(fluralaner for extended-release
injectable suspension)

For subcutaneous use in dogs only

CAUTION:
Federal law restricts this drug to use by or on the order of a licensed veterinarian.

- 1 vial of sterile fluralaner (150 mg fluralaner per mL when constituted)
- 1 vial of sterile vehicle
- 1 vent needle

For use in dogs and puppies 6 months of age and older
Approved by FDA under NADA # 141-599

MERCK
Animal Health